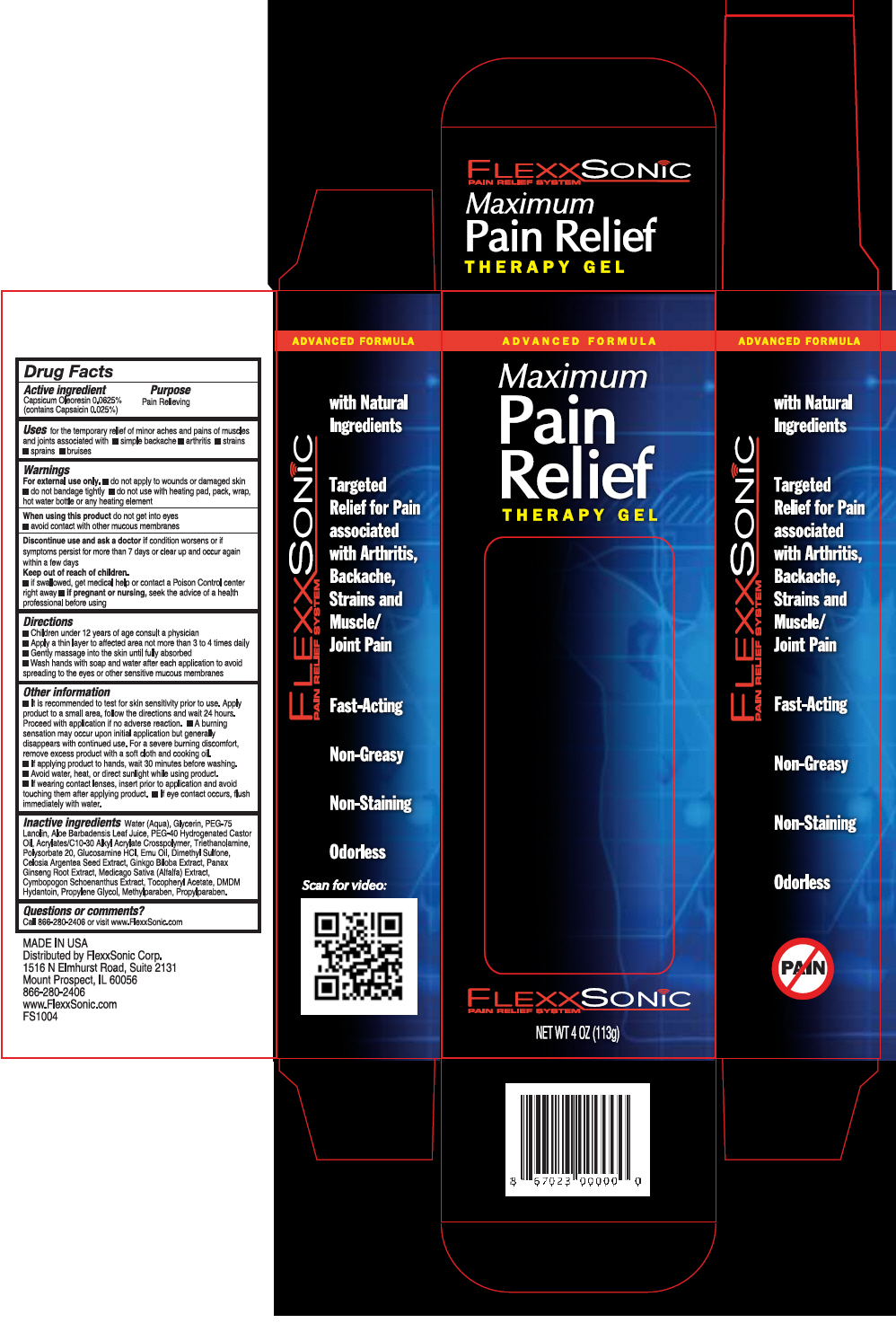 DRUG LABEL: FlexxSonic 
NDC: 69397-156 | Form: GEL
Manufacturer: Flexxsonic Corporation
Category: otc | Type: HUMAN OTC DRUG LABEL
Date: 20150731

ACTIVE INGREDIENTS: Capsaicin 0.25 mg/1 g
INACTIVE INGREDIENTS: Water; Glycerin; PEG-75 LANOLIN; DIMETHYL SULFONE; ALOE VERA LEAF; ALFALFA LEAF; CYMBOPOGON SCHOENANTHUS LEAF; GLUCOSAMINE HYDROCHLORIDE; GINKGO; POLYSORBATE 20; EMU OIL; DMDM HYDANTOIN; PROPYLENE GLYCOL; METHYLPARABEN; PROPYLPARABEN; ASIAN GINSENG; .ALPHA.-TOCOPHEROL ACETATE; POLYOXYL 40 HYDROGENATED CASTOR OIL; TROLAMINE

FlexxSonic
Pain Relief

Drug Facts

Active ingredient

Capsicum Oleoresin 0.0625% (contains Capsaicin 0.025%)

Purpose

Pain Relieving

Uses

for the temporary relief of minor aches and pains of muscles and joints associated with

- simple backache
- arthritis
- strains
- sprains
- bruises

Warnings

For external use only.

- do not apply to wounds or damaged skin
- do not bandage tightly
- do not use with heating pad, pack, wrap, hot water bottle or any heating element When using this product do not get into eyes
- avoid contact with other mucous membranes Discontinue use and ask a doctor if condition worsens or if symptoms persist for more than 7 days or clear up and occur again within a few days

Keep out of reach of children.

- if swallowed, get medical help or contact a Poison Control center right away
- if pregnant or nursing, seek the advice of a health professional before using

Directions

- Children under 12 years of age consult a physician
- Apply a thin layer to affected area not more than 3 to 4 times daily
- Gently massage into the skin until fully absorbed
- Wash hands with soap and water after each application to avoid spreading to the eyes or other sensitive mucous membranes

Other information

- It is recommended to test for skin sensitivity prior to use. Apply product to a small area, follow the directions and wait 24 hours. Proceed with application if no adverse reaction.
- A burning sensation may occur upon initial application but generally disappears with continued use. For a severe burning discomfort, remove excess product with a soft cloth and cooking oil.
- If applying product to hands, wait 30 minutes before washing.
- Avoid water, heat, or direct sunlight while using product.
- If wearing contact lenses, insert prior to application and avoid touching them after applying product.
- If eye contact occurs, flush immediately with water.

Inactive ingredients

Water (Aqua), Glycerin, PEG-75 Lanolin, Aloe Barbadensis Leaf Juice, PEG-40 Hydrogenated Castor Oil, Acrylates/C10-30 Alkyl Acrylate Crosspolymer, Triethanolamine, Polysorbate 20, Glucosamine HCI, Emu Oil, Dimethyl Sulfone, Celosia Argentea Seed Extract, Ginkgo Biloba Extract, Panax Ginseng Root Extract, Medicago Saliva (Alfalfa) Extract, Cymbopogon Schoenanthus Extract, Tocopheryl Acetate, DMDM Hydantoin, Propylene Glycol, Methylparaben, Propylparaben.

Questions or comments?

Call 866-280-2406 or visit www.FlexxSonic.com

Distributed by FlexxSonic Corp.
1516 N Elmhurst Road, Suite 2131
Mount Prospect, IL 60056

PRINCIPAL DISPLAY PANEL - 113 g Bottle Carton

ADVANCED FORMULA

Maximum
Pain
Relief
THERAPY GEL

FLEXXSONiC
PAIN RELIEF SYSTEM

NET WT 4 OZ (113g)